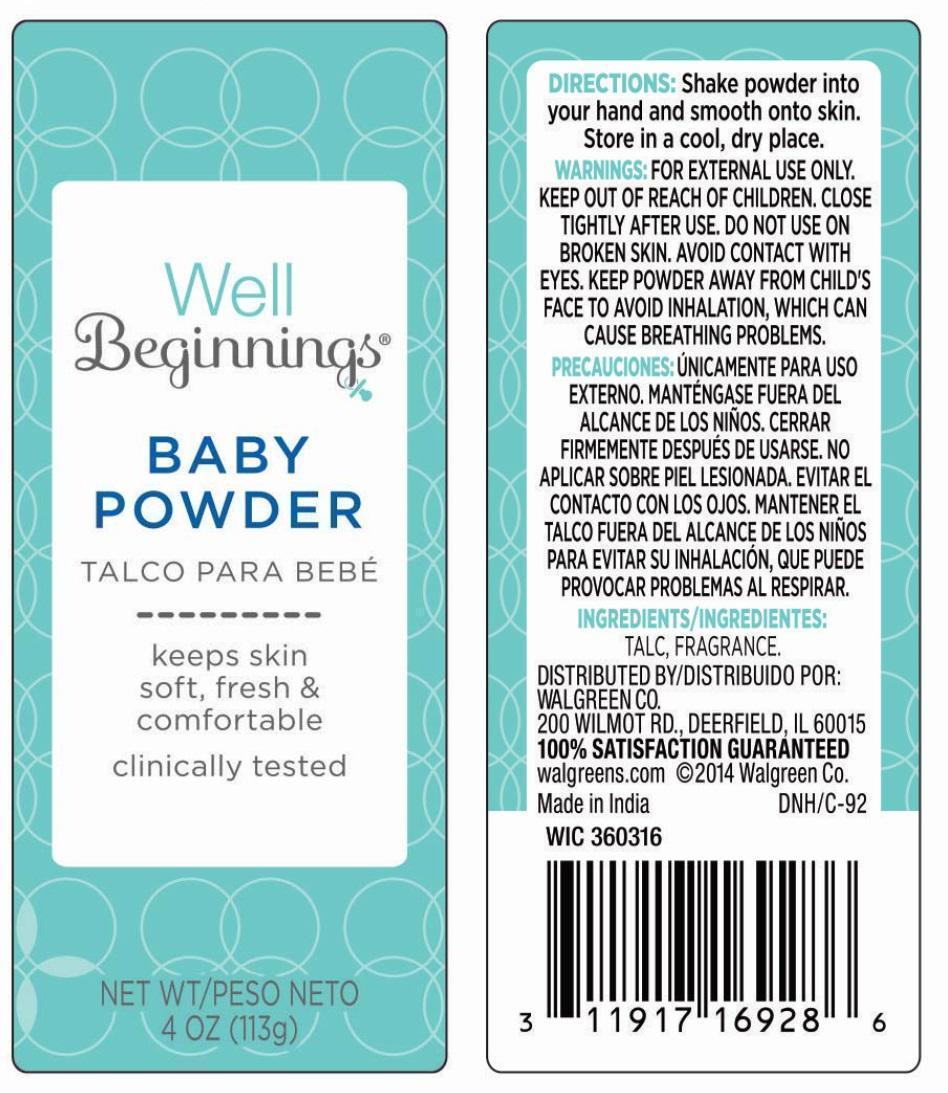 DRUG LABEL: Baby
NDC: 0363-0901 | Form: POWDER
Manufacturer: Walgreen Company
Category: otc | Type: HUMAN OTC DRUG LABEL
Date: 20200813

ACTIVE INGREDIENTS: TALC 100 g/100 g
INACTIVE INGREDIENTS: FRAGRANCE CLEAN ORC0600327 0.1 g/100 g

BABY POWDER

Active ingredient

Talc 100%

Purpose

Skin Protectant

Uses
Keeps skin soft, fresh & comfortable.

Warnings

For external use only.

Keep out of reach of children

Close tightly after use.

Do not use on broken skin.

Avoid contact with eyes.

Keep powder away from child’s face to avoid inhalation, which can cause breathing problems.

Directions

Shake powder into your hand and smooth onto skin.

Storage

Store in a cool, dry place.

Inactive ingredient

Fragrance

Package/Label Principal Display Panel

Baby Powder

Keeps skin soft, fresh & comfortable

Clinically Tested

NET WT 4 OZ (113 g)